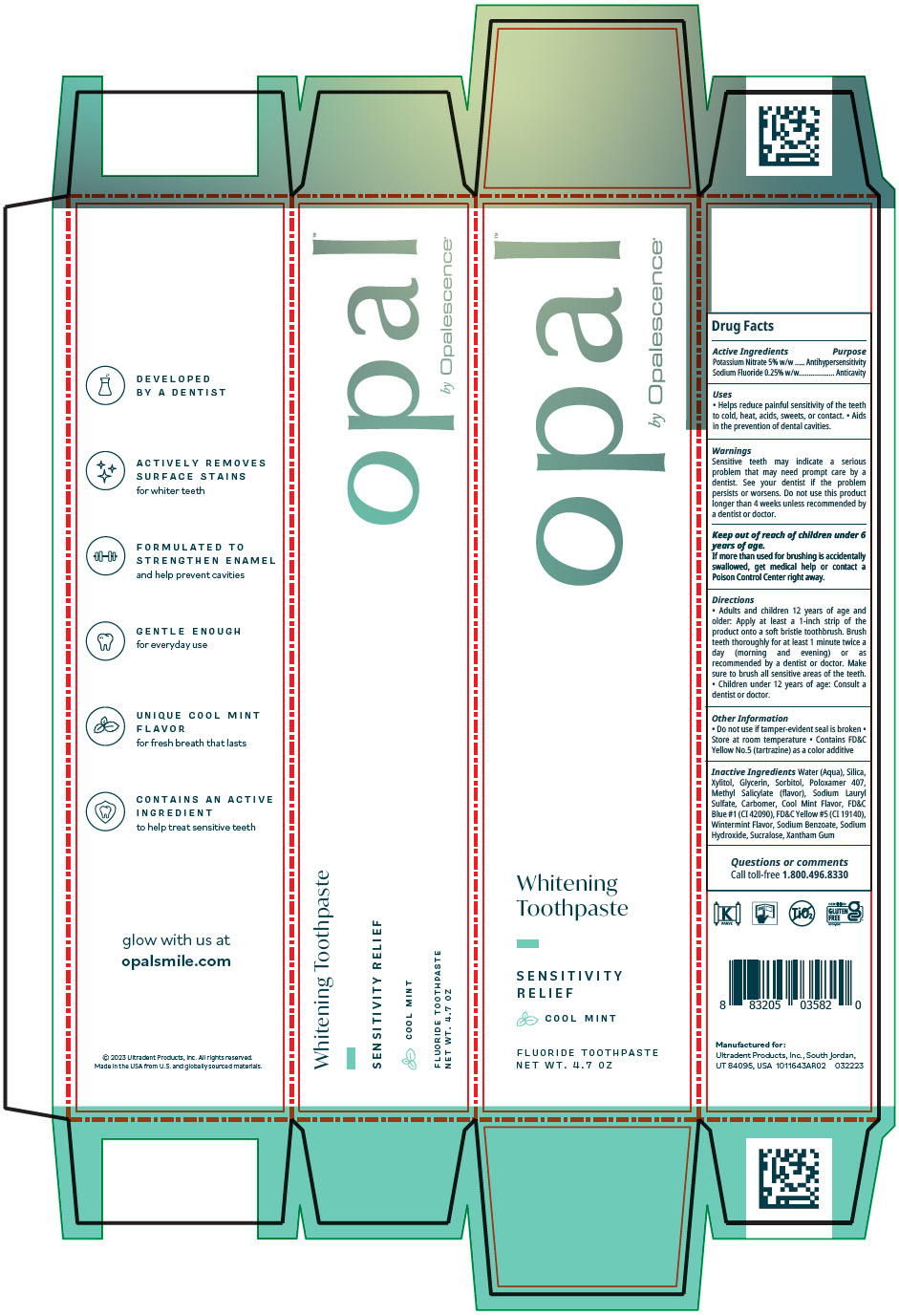 DRUG LABEL: Opal by Opalescence Sensitivity
NDC: 51206-311 | Form: GEL, DENTIFRICE
Manufacturer: Ultradent Products, Inc.
Category: otc | Type: HUMAN OTC DRUG LABEL
Date: 20250617

ACTIVE INGREDIENTS: POTASSIUM NITRATE 50 mg/1 g; SODIUM FLUORIDE 1.1 mg/1 g
INACTIVE INGREDIENTS: SILICON DIOXIDE; XYLITOL; WATER; GLYCERIN; SORBITOL; POLOXAMER 407; METHYL SALICYLATE; SODIUM LAURYL SULFATE; CARBOMER HOMOPOLYMER TYPE B (ALLYL PENTAERYTHRITOL CROSSLINKED); FD&C BLUE NO. 1; FD&C YELLOW NO. 5; SODIUM BENZOATE; SODIUM HYDROXIDE; SUCRALOSE; XANTHAN GUM

Opal™ by Opalescence®Sensitivity

Drug Facts

ACTIVE INGREDIENT

Active Ingredients | Purpose
Potassium Nitrate 5% w/w | Antihypersensitivity
Sodium Fluoride 0.25% w/w | Anticavity

Uses

- Helps reduce painful sensitivity of the teeth to cold, heat, acids, sweets, or contact.
- Aids in the prevention of dental cavities.

Warnings

Sensitive teeth may indicate a serious problem that may need prompt care by a dentist. See your dentist if the problem persists or worsens. Do not use this product longer than 4 weeks unless recommended by a dentist or doctor.

Keep out of reach of children under 6 years of age.

If more than used for brushing is accidentally swallowed, get medical help or contact a Poison Control Center right away.

Directions

- Adults and children 12 years of age and older: Apply at least a 1-inch strip of the product onto a soft bristle toothbrush. Brush teeth thoroughly for at least 1 minute twice a day (morning and evening) or as recommended by a dentist or doctor. Make sure to brush all sensitive areas of the teeth.
- Children under 12 years of age: Consult a dentist or doctor.

Other Information

- Do not use if tamper-evident seal is broken
- Store at room temperature
- Contains FD&C Yellow No.5 (tartrazine) as a color additive

Inactive Ingredients

Water (Aqua), Silica, Xylitol, Glycerin, Sorbitol, Poloxamer 407, Methyl Salicylate (flavor), Sodium Lauryl Sulfate, Carbomer, Cool Mint Flavor, FD&C Blue #1 (CI 42090), FD&C Yellow #5 (CI 19140), Wintermint Flavor, Sodium Benzoate, Sodium Hydroxide, Sucralose, Xantham Gum

Questions or comments

Call toll-free 1.800.496.8330

PRINCIPAL DISPLAY PANEL - 4.7 OZ Tube Carton

opal™
by Opalescence®

Whitening
Toothpaste

SENSITIVITY
RELIEF

COOL MINT

FLUORIDE TOOTHPASTE
NET WT. 4.7 OZ